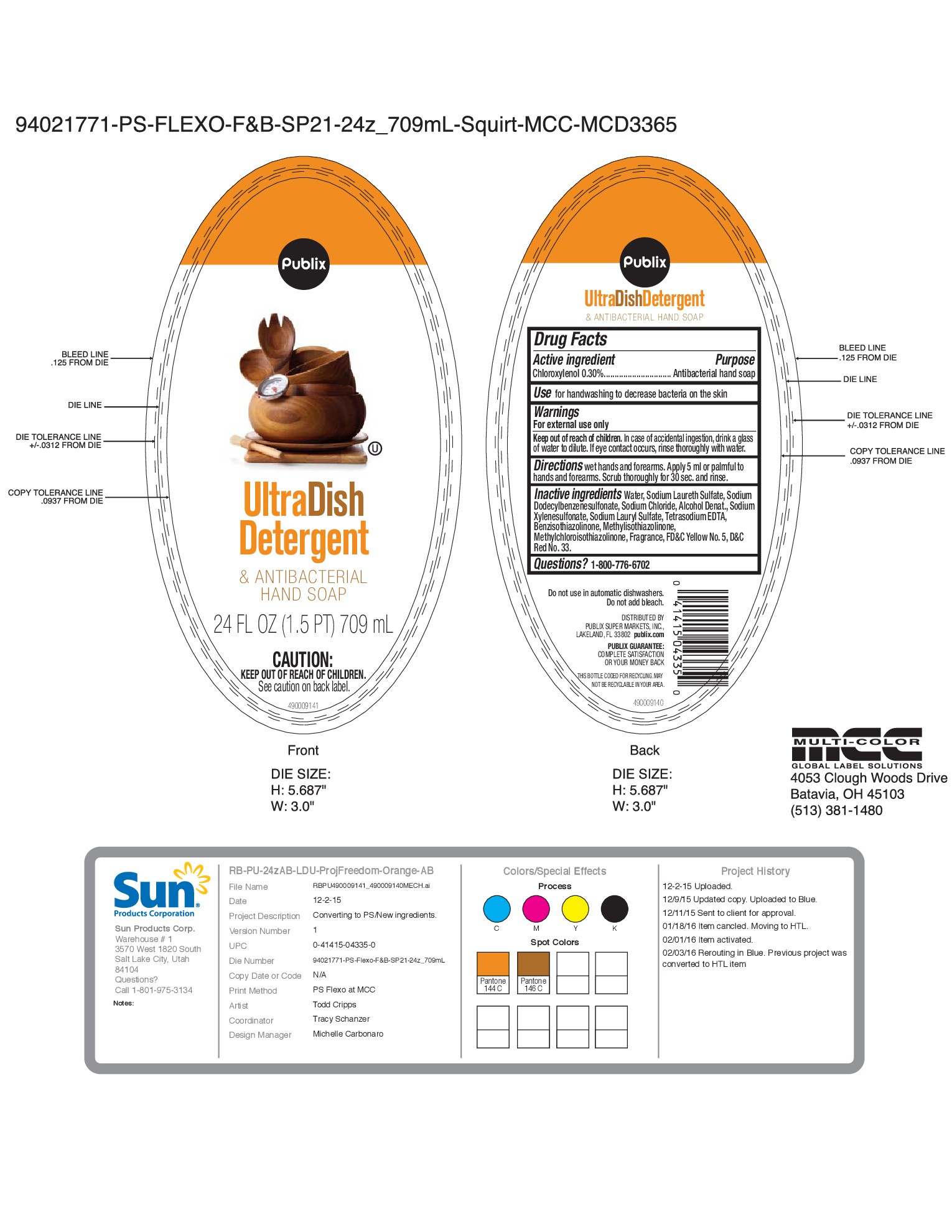 DRUG LABEL: Publix Ultra Dish Detergent Orange
NDC: 63691-032 | Form: SOAP
Manufacturer: Sun Products Corporation
Category: otc | Type: HUMAN OTC DRUG LABEL
Date: 20160630

ACTIVE INGREDIENTS: CHLOROXYLENOL 0.3 g/100 mL
INACTIVE INGREDIENTS: METHYLCHLOROISOTHIAZOLINONE; FD&C YELLOW NO. 5; SODIUM CHLORIDE; WATER; SODIUM LAURETH SULFATE; SODIUM DODECYLBENZENESULFONATE; EDETATE SODIUM; ALCOHOL; BENZISOTHIAZOLINONE; SODIUM XYLENESULFONATE; SODIUM LAURYL SULFATE; METHYLISOTHIAZOLINONE; D&C RED NO. 33

Publix

Ultra Dish Detergent

& Antibacterial Hand Soap

Active ingredient

Chloroxylenol 0.30%

Purpose

Antibacterial hand soap

Use

for handwashing to decrease bacteria on the skin

Warnings

For external use only

Keep out of reach of children

In case of accidental ingestion, drink a glass of water to dilute. If eye contact occurs, rinse thoroughly with water.

Directions

wet hands and forearms. Apply 5 ml or palmful to hands and forearms. Scrub thoroughly for 30 sec. and rinse.

Inactive ingredients

Water, Sodium Laureth Sulfate, Sodium Dodecylbenzenesulfonate, Sodium Chloride, Alcohol Denat., Sodium Xylenesulfonate, Sodium Lauryl Sulfate, Tetrasodium EDTA, Benzisothiazolinone, Methyisothiazolinone, Methychloroisothiazolinone, Fragrance, FD&C Yellow No. 5, D&C Red No. 33

Questions?

1-800-776-6702